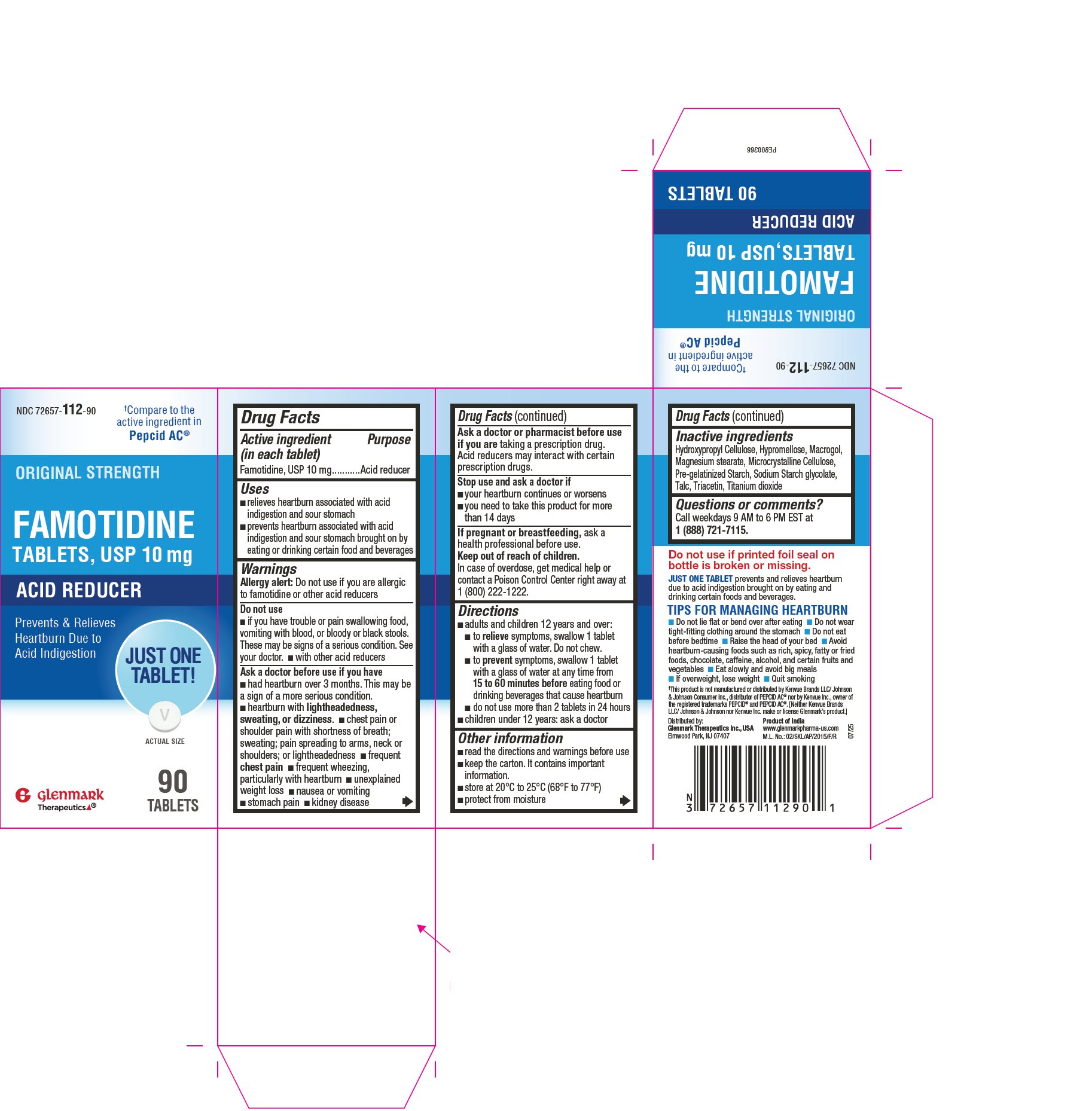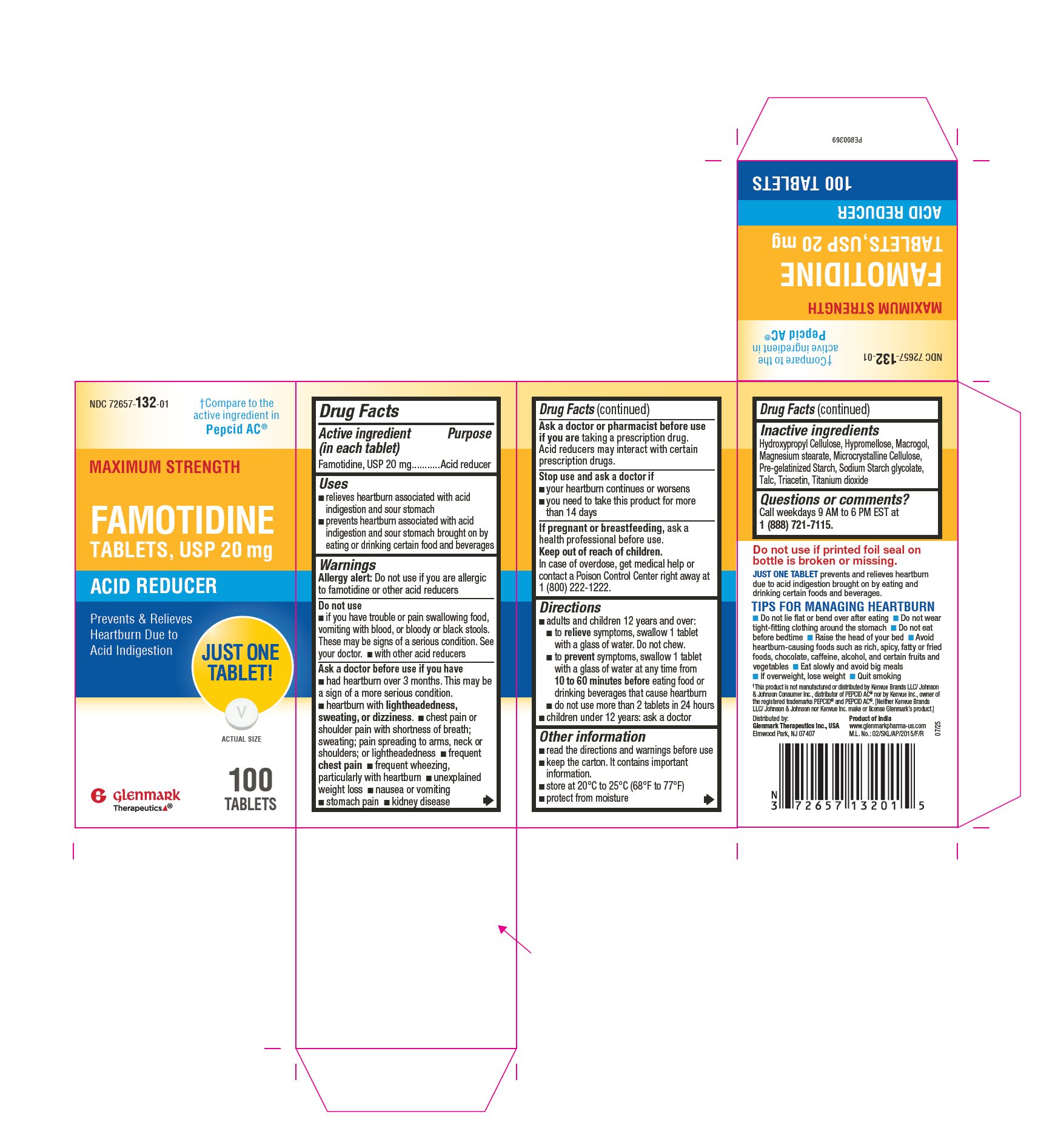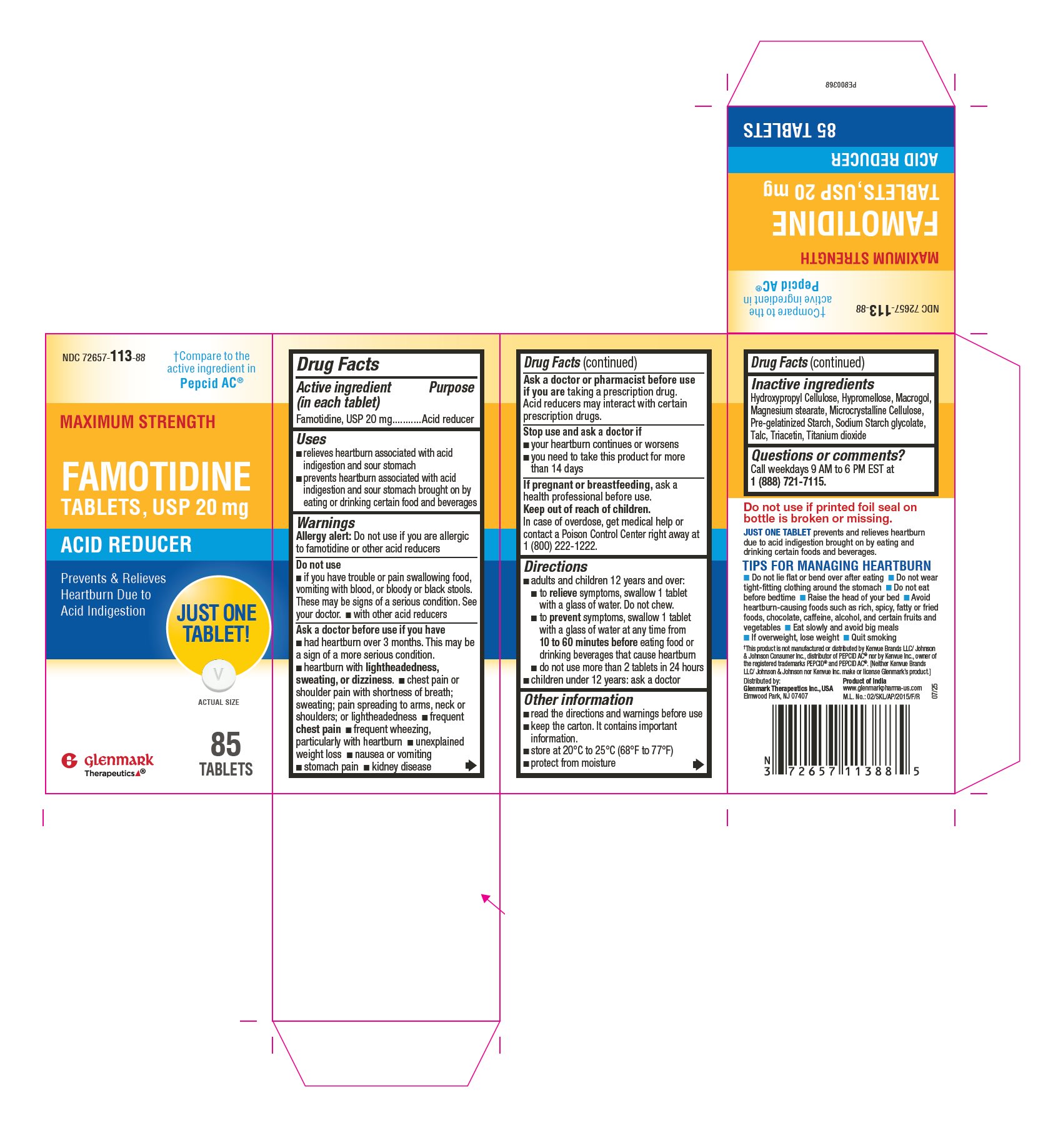 DRUG LABEL: Famotidine
NDC: 72657-112 | Form: TABLET, FILM COATED
Manufacturer: GLENMARK THERAPEUTICS INC., USA
Category: otc | Type: HUMAN OTC DRUG LABEL
Date: 20260113

ACTIVE INGREDIENTS: FAMOTIDINE 10 mg/1 1
INACTIVE INGREDIENTS: MICROCRYSTALLINE CELLULOSE; STARCH, CORN; SODIUM STARCH GLYCOLATE TYPE A; HYDROXYPROPYL CELLULOSE (110000 WAMW); MAGNESIUM STEARATE; HYPROMELLOSE 2910 (6 MPA.S); TITANIUM DIOXIDE; TRIACETIN; POLYETHYLENE GLYCOL 4000; TALC

Famotidine Tablets

Drug Facts

Active ingredient (in each tablet)

Famotidine, USP 10 mg and 20 mg

Purpose

Acid reducer

Uses

- relieves heartburn associated with acid indigestion and sour stomach
- prevents heartburn associated with acid indigestion and sour stomach brought on by eating or drinking certain food and beverages

Warnings

Allergy alert

Do not use if you are allergic to famotidine or other acid reducers

Do not use

- if you have trouble or pain swallowing food, vomiting with blood, or bloody or black stools. These may be signs of a serious condition. See your doctor.
- with other acid reducers

Ask a doctor before use if you have

- had heartburn over 3 months. This may be a sign of a more serious condition.
- heartburn with lightheadedness, sweating, or dizziness
- chest pain or shoulder pain with shortness of breath; sweating; pain spreading to arms, neck or shoulders; or lightheadedness
- frequent chest pain
- frequent wheezing, particularly with heartburn
- unexplained weight loss
- nausea or vomiting
- stomach pain
- kidney disease

Ask a doctor or pharmacist before use if you are taking a prescription drug. Acid reducers may interact with certain prescription drugs.

Stop use and ask a doctor if

- your heartburn continues or worsens
- you need to take this product for more than 14 days

PREGNANCY OR BREAST FEEDING

If pregnant or breast-feeding, ask a health professional before use.

Keep out of reach of children. In case of overdose, get medical help or contact a Poison Control Center right away. 1 (800) 222-1222.

Directions

- adults and children 12 years and over:
  - to relieve symptoms, swallow 1 tablet with a glass of water. Do not chew.
  - to prevent symptoms, swallow 1 tablet (of 10 mg) with a glass of water at any time from 15 to 60 minutes before eating food or drinking beverages that cause heartburn
  - to prevent symptoms, swallow 1 tablet (of 20 mg) with a glass of water at any time from 10 to 60 minutes before eating food or drinking beverages that cause heartburn
  - before eating food or drinking beverages that cause heartburn
  - do not use more than 2 tablets in 24 hours
- children under 12 years: ask a doctor

Other information

- read the directions and warnings before use
- keep the carton. It contains important information.
- store at 20°C to 25°C (68°F to 77°F)
- protect from moisture

Inactive ingredients

Hydroxypropyl Cellulose, Hypromellose, , Macrogol, Magnesium stearate, Microcrystalline Cellulose, Pre-gelatinized Starch, Sodium Starch glycolate, Talc, Triacetin, Titanium dioxide

Questions or comments?

Call weekdays 9 AM to 6 PM EST at 1 (888) 721-7115.

Do not use if printed foil seal on bottle is broken or missing.

JUST ONE TABLET prevents and relieves heartburn due to acid indigestion brought on by eating and drinking certain foods and beverages.

TIPS FOR MANAGING HEARTBURN

􀀁 Do not lie ﬂat or bend over after eating 􀀁 Do not wear tight-ﬁtting clothing around the stomach

􀀁 Do not eat before bedtime 􀀁 Raise the head of your bed 􀀁 Avoid heartburn-causing foods such as rich, spicy, fatty or fried foods, chocolate, caffeine, alcohol, and certain fruits and vegetables 􀀁 Eat slowly and avoid big meals 􀀁 If overweight, lose weight 􀀁 Quit smoking

Distributed by: Glenmark Therapeutics Inc., USA
Elmwood Park, NJ 07407
Made in India
M.L. No.: 02/SKL/AP/2015/F/R
Revision: 07/25

Principal Display Panel

NDC 72657-112-90

Famotidine Tablets, USP 10mg

90 Tablets

Principal Display Panel

NDC 72657-113-88

Famotidine Tablets, USP 20mg

85 Tablets

Principal Display Panel

NDC 72657-132-01

Famotidine Tablets, USP 20mg

100 Tablets